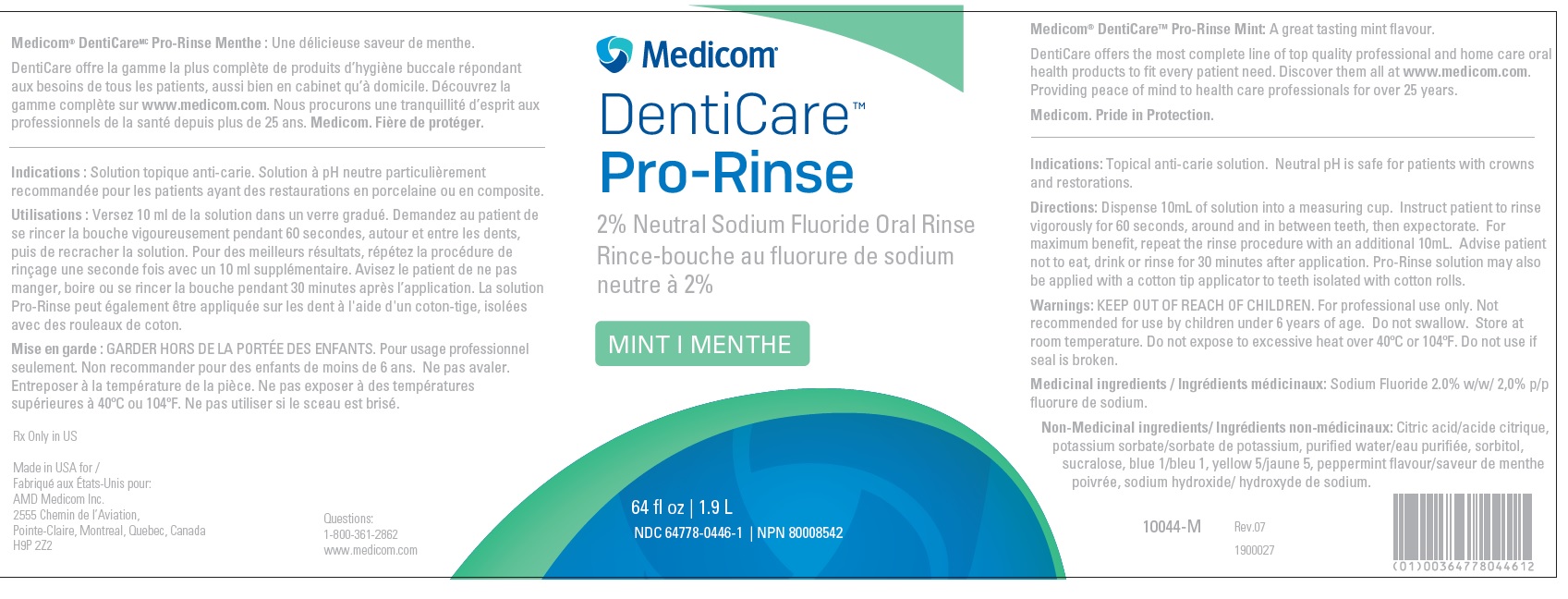 DRUG LABEL: Denti-Care Denti-Rinse
NDC: 64778-0446 | Form: LIQUID
Manufacturer: AMD Medicom
Category: prescription | Type: HUMAN PRESCRIPTION DRUG LABEL
Date: 20210127

ACTIVE INGREDIENTS: SODIUM FLUORIDE 0.02 g/1 mL

10044-M Mint Rinse
DentiCare Pro-Rinse 2 % Neutral Sodium Fluoride Oral Rinse

General Information

AMD Medicom Inc.
DentiCare Pro-Rinse
2% Neutral Sodium Fluoride Oral Rinse
Mint
1.9 L / 64 fl oz
NDC 64778-0446-1
NPN 80008542
Item code 10044-M

Indications and Directions

Indications: Topical anti-carie solution. Neutral pH is safe for patients with crowns and restorations.

Directions: Dispense 10mL of solution into a measuring cup. Instruct patient to rinse vigorously for 60 seconds, around and in between teeth, then expectorate. For maximum benefit, repeat the rinse procedure with an additional 10mL.

Advise patient not to eat, drink or rinse for 30 minutes after application.

Pro-Rinse solution may also be applied with a cotton tip applicator to teeth isolated with cotton rolls

Non-Medicinal Ingredients

Citric acid, potassium sorbate, purified water, sorbitol, sucralose, blue 1, yellow 5, peppermint flavour, sodium hydroxide

Warnings

KEEP OUT OF REACH OF CHILDREN. For professional use only.

Not recommended for use by children under 6 years of age.

Do not swallow.

Store at room temperature. Do not expose to excessive heat over 40ºC or 104ºF.

Do not use if seal is broken.

Contact Information

Rx Only in US

Made in USA for AMD Medicom Inc.
2555 Chemin de l’Aviation,
Pointe-Claire, Quebec, Canada
H9P 2Z2

Questions: 1-800-361-2862

www.medicom.com